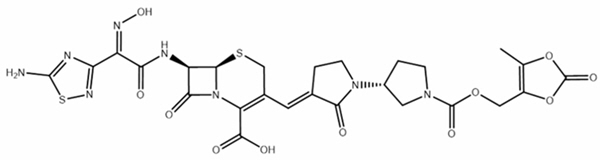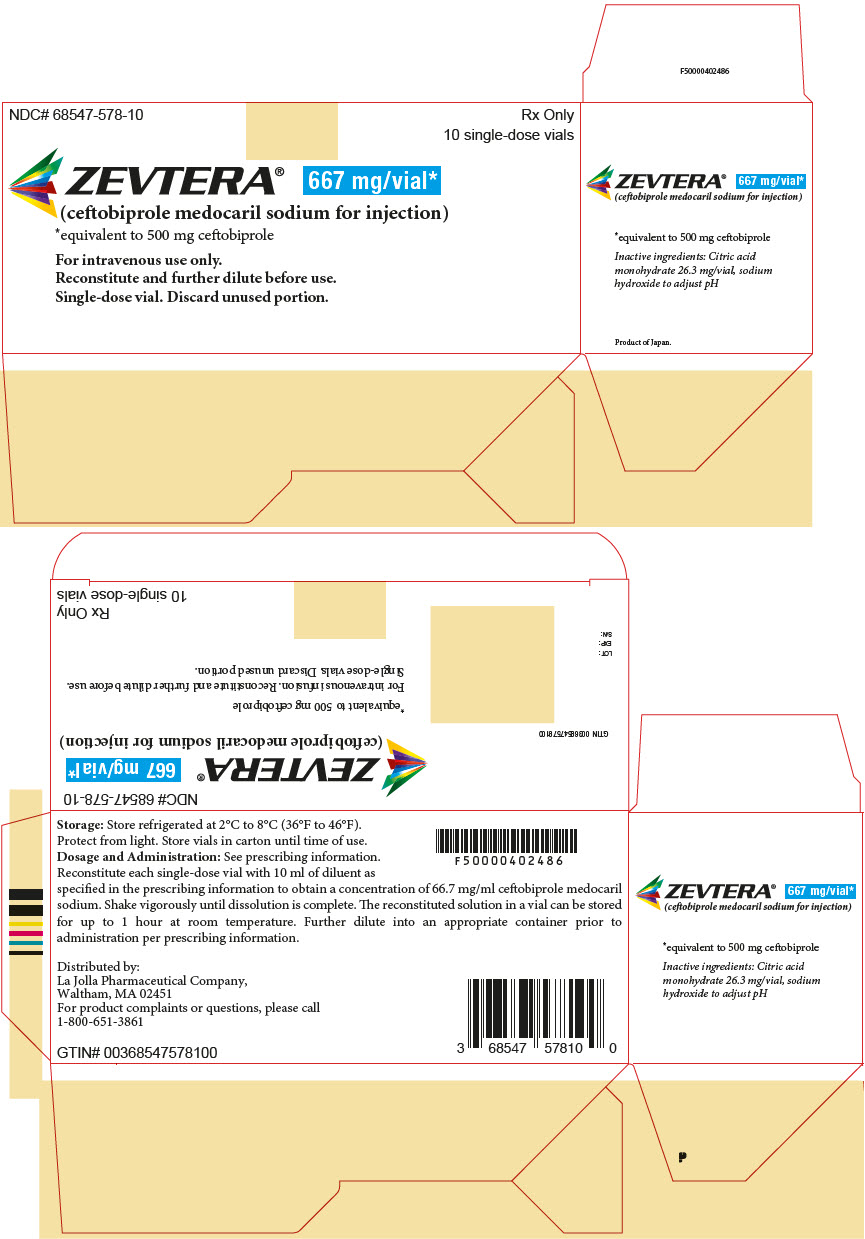 DRUG LABEL: ZEVTERA
NDC: 68547-578 | Form: INJECTION, POWDER, FOR SOLUTION
Manufacturer: La Jolla Pharmaceutical Company
Category: prescription | Type: HUMAN PRESCRIPTION DRUG LABEL
Date: 20251209

ACTIVE INGREDIENTS: ceftobiprole medocaril sodium 667 mg/1 1
INACTIVE INGREDIENTS: citric acid monohydrate; sodium hydroxide

HIGHLIGHTS OF PRESCRIBING INFORMATION

These highlights do not include all the information needed to use ZEVTERA safely and effectively. See full prescribing information for ZEVTERA.
ZEVTERA® (ceftobiprole medocaril sodium for injection), for intravenous use
Initial U.S. Approval: 2024

1 INDICATIONS AND USAGE

ZEVTERA is a cephalosporin antibacterial indicated for the treatment of:

- Adult patients with Staphylococcus aureus bloodstream infections (bacteremia) (SAB), including those with right-sided infective endocarditis (1.1),
- Adult patients with acute bacterial skin and skin structure infections (ABSSSI) (1.2), and
- Adult and pediatric patients (3 months to less than 18 years old) with community-acquired bacterial pneumonia (CABP) (1.3).

To reduce the development of drug-resistant bacteria and maintain the effectiveness of ZEVTERA and other antibacterial drugs, ZEVTERA should be used only to treat or prevent infections that are proven or strongly suspected to be caused by bacteria (1.4).

2 DOSAGE AND ADMINISTRATION

- The recommended dosage of ZEVTERA for adult patients with SAB, ABSSSI and CABP is described in the table below (2.1):
  Indication in Adults | Dose | Frequency
  SAB | 667 mg | Every 6 hours on Days 1 to 8
  SAB | 667 mg | Every 8 hours from Day 9
  ABSSSI | 667 mg | Every 8 hours
  CABP | 667 mg | Every 8 hours

- Duration of treatment in adult patients is up to 42 days for SAB and 5 days to 14 days for ABSSSI and CABP (2.1).
- Administer each prepared intravenous infusion solution of ZEVTERA over 2 hours at a concentration of 2.67 mg/mL (2.1, 2.6).
- The recommended dosage of ZEVTERA for pediatric patients (3 months to less than 18 years old) with CABP is described below (2.2).
  Pediatric Age Group for CABP | Dose | Frequency
  12 years to less than 18 years old | 13.3 mg/kg (up to 667 mg/dose) | Every 8 Hours
  Greater than or equal to 3 months and less than 12 years old | 20 mg/kg (up to 667 mg/dose) | Every 8 Hours

- Duration of treatment in pediatric patients is 7 days to 14 days for CABP (2.1).
- Administer each prepared intravenous infusion solution of ZEVTERA over 2 hours at a concentration of 2.67 mg/mL for pediatric patients aged 12 years to less than 18 years old and at a concentration of 5.33 mg/mL for pediatric patients aged 3 months to less than 12 years old (2.2, 2.6).
- Reduce the dosage in adult patients with CLCR less than 50 mL/min, including patients with CLCR less than 15 mL/min on hemodialysis (2.3 and 8.6).
- Increase the dosage in adult patients with CLCR greater than 150 mL/min (2.3).
- Reduce the dosage in pediatric patients aged 2 years old to less than 18 years old with eGFR less than 50 mL/min/1.73 m^2 and greater than or equal to 15 mL/min/1.73 m^2 (2.4 and 8.6).
- See Full Prescribing Information for instructions for preparation of ZEVTERA solution infusion solution (2.5).

3 DOSAGE FORMS AND STRENGTHS

For injection: 667 mg of ceftobiprole medocaril sodium (equivalent to 500 mg of ceftobiprole) as a lyophilized powder for reconstitution in a single-dose vial (3).

4 CONTRAINDICATIONS

ZEVTERA is contraindicated in patients with a known history of severe hypersensitivity to ZEVTERA, or to other members of the cephalosporin class (4).

5 WARNINGS AND PRECAUTIONS

- Increased Mortality with Unapproved use in Ventilator-Associated Bacterial Pneumonia (VABP) Patients: The safety and effectiveness of ZEVTERA for the treatment of VABP has not been established and the use of ZEVTERA for VABP is not approved (5.1).
- Hypersensitivity Reactions: Discontinue ZEVTERA if a hypersensitivity reaction occurs, and institute appropriate treatment (5.2).
- Seizures and other adverse central nervous system (CNS) reactions have been associated with the use of ZEVTERA. If seizures or other CNS adverse reactions occur, evaluate patients to determine whether ZEVTERA should be discontinued (5.3).
- Clostridioides difficile-associated diarrhea (CDAD) has been reported with nearly all systemic antibacterial agents, including ZEVTERA. Evaluate if diarrhea occurs (5.4).

6 ADVERSE REACTIONS

- SAB (adult patients): The most common adverse reactions occurring in ≥ 4% of adult patients were anemia, nausea, hypokalemia, vomiting, hepatic enzyme and bilirubin increased, diarrhea, blood creatinine increased, hypertension, leukopenia, and pyrexia (6.1).
- ABSSSI (adult patients): The most common adverse reactions occurring in ≥ 2% of adult patients were nausea, diarrhea, headache, injection site reaction, hepatic enzyme increased, rash, vomiting, and dysgeusia (6.1).
- CABP (adult and pediatric patients 3 months to less than 18 years of age):
  - Adult Patients: The most common adverse reactions occurring in ≥ 2% of adult patients were nausea, hepatic enzyme increased, vomiting, diarrhea, headache, rash, insomnia, abdominal pain, phlebitis, hypertension, and dizziness (6.1).
  - Pediatric Patients: The most common adverse reactions occurring in ≥ 2% of pediatric patients were vomiting, headache, hepatic enzyme increased, diarrhea, infusion site reaction, phlebitis and pyrexia (6.1).

To report SUSPECTED ADVERSE REACTIONS, contact ISTx, LLC at 1-800-651-3861 or FDA at 1-800-FDA-1088 or www.fda.gov/medwatch.

7 DRUG INTERACTIONS

Organic Anion Transporting Polypeptide 1B1/1B3 (OATP1B1/OATP1B3) Substrates: ZEVTERA may increase the plasma concentrations of OATP1B1 and OATP1B3 substrates. Concomitant administration is not recommended (7.1)

FULL PRESCRIBING INFORMATION

1 INDICATIONS AND USAGE

1.1 Staphylococcus aureus Bloodstream Infection (Bacteremia)

ZEVTERA is indicated for the treatment of adult patients with Staphylococcus aureus bloodstream infection (bacteremia) (SAB), including those with right-sided infective endocarditis, caused by methicillin-susceptible and methicillin-resistant isolates.

1.2 Acute Bacterial Skin and Skin Structure Infections

ZEVTERA is indicated for the treatment of adult patients with acute bacterial skin and skin structure infections (ABSSSI) caused by susceptible isolates of the following gram-positive and gram-negative microorganisms: Staphylococcus aureus (methicillin-susceptible and methicillin-resistant isolates), Streptococcus pyogenes, and Klebsiella pneumoniae.

1.3 Community-Acquired Bacterial Pneumonia

ZEVTERA is indicated for the treatment of adult and pediatric patients (3 months to less than 18 years old) with community-acquired bacterial pneumonia (CABP) caused by susceptible isolates of the following gram-positive and gram-negative microorganisms: Staphylococcus aureus (methicillin-susceptible isolates), Streptococcus pneumoniae, Haemophilus influenzae, Haemophilus parainfluenzae, Escherichia coli, and Klebsiella pneumoniae.

1.4 Usage

To reduce the development of drug-resistant bacteria and maintain the effectiveness of ZEVTERA and other antibacterial drugs, ZEVTERA should be used only to treat or prevent infections that are proven, or strongly suspected, to be caused by susceptible bacteria. When culture and susceptibility information are available, they should be considered in selecting or modifying antibacterial therapy. In the absence of such data, local epidemiology and susceptibility patterns may contribute to the empiric selection of therapy.

2 DOSAGE AND ADMINISTRATION

2.1 Recommended Dosage and Administration for SAB, ABSSSI and CABP in Adult Patients

The recommended dosage of ZEVTERA for the treatment of adult patients with SAB, ABSSSI and CABP is described in Table 1. The duration of treatment in adult patients is up to 42 days for SAB and 5 days to 14 days for ABSSSI and CABP.

Administer each prepared intravenous infusion solution of ZEVTERA over 2 hours at a concentration of 2.67 mg/mL to adult patients [see Dosage and Administration (2.5)].

Table 1: Recommended Dosage Regimen for SAB, ABSSSI and CABP in Adult Patients
Indication [Duration of treatment in adult patients is up to 42 days for SAB and 5 days to 14 days for ABSSSI and CABP.] | Dose | Frequency [Administer each prepared intravenous infusion solution of ZEVTERA over 2 hours at a concentration of 2.67 mg/mL [see Dosage and Administration (2.5)]]
SAB | 667 mg [667 mg of ceftobiprole medocaril sodium is equivalent to 500 mg of ceftobiprole.] | Every 6 hours on Days 1 to 8
SAB | 667 mg [667 mg of ceftobiprole medocaril sodium is equivalent to 500 mg of ceftobiprole.] | Every 8 hours from Day 9
ABSSSI | 667 mg | Every 8 hours
CABP | 667 mg | Every 8 hours

2.2 Recommended Dosage and Administration for CABP in Pediatric Patients (3 months to less than 18 years old)

For treatment of pediatric patients with CABP, the recommended dosage of ZEVTERA is described in Table 2, based on patient age and weight [see Clinical Pharmacology (12.3)]. The duration of treatment for CABP in pediatric patients (3 months to less than 18 years old) is 7 days to 14 days.

Administer each prepared intravenous infusion solution of ZEVTERA over 2 hours at a concentration of 2.67 mg/mL for patients 12 years to less than 18 years old and at a concentration of 5.33 mg/mL for patients greater than or equal to 3 months to less than 12 years old [see Dosage and Administration (2.5)].

Table 2: Recommended Dosage Regimen in Pediatric Patients with CABP
Pediatric Age Group | Dose [Duration of treatment for CABP in pediatric patients is 7 days to 14 days.] | Frequency
12 years to less than 18 years old | 13.3 mg/kg (up to 667 mg/dose [13.3 mg/kg of ceftobiprole medocaril sodium is equivalent to 10 mg/kg of ceftobiprole; 20 mg/kg ceftobiprole medocaril sodium is equivalent to 15 mg/kg of ceftobiprole. 667 mg ceftobiprole medocaril sodium is equivalent to 500 mg of ceftobiprole.]) | Every 8 Hours [Administer each prepared intravenous infusion solution of ZEVTERA over 2 hours at a concentration of 2.67 mg/mL for patients 12 years to less than 18 years old [see Dosage and Administration (2.5)].]
3 months to less than 12 years old | 20 mg/kg (up to 667 mg/dose) | Every 8 Hours [Administer each prepared intravenous infusion solution of ZEVTERA over 2 hours at a concentration of 5.33 mg/mL for patients greater than or equal to 3 months to less than 12 years old [see Dosage and Administration (2.5)].]

2.3 Recommended Dosage Regimen in Adult Patients with Renal Impairment

The recommended ZEVTERA dosage in adult patients with renal impairment (CLCR less than 50 mL/min), including patients receiving hemodialysis is shown in Table 3. The duration of treatment in adult patients with renal impairment is up to 42 days for SAB and 5 days to 14 days for ABSSSI and CABP.

Administer each prepared intravenous infusion solution of ZEVTERA over 2 hours at a concentration of 2.67 mg/mL to adult patients with renal impairment [see Dosage and Administration (2.5)].

In adult patients with augmented renal clearance (CLCR greater than 150 mL/min), increase the ZEVTERA dosage to 667 mg every 6 hours.

Table 3: ZEVTERA Recommended Dosage Regimens for SAB, ABSSSI and CABP in Adult Patients with Renal Impairment
Indication [Duration of treatment in adult patients is up to 42 days for SAB and 5 days to 14 days for ABSSSI and CABP.] | Creatinine Clearance, CLCR (mL/min) [Based on calculated creatinine clearance [see Use in Specific Populations (8.6)].] | Dose [667 mg ceftobiprole medocaril sodium is equivalent to 500 mg of ceftobiprole; 333 mg ceftobiprole medocaril sodium is equivalent to 250 mg of ceftobiprole.] | Frequency [Administer each prepared intravenous infusion solution of ZEVTERA over 2 hours at a concentration of 2.67 mg/mL [see Dosage and Administration (2.5)].]
SAB | 30 to less than 50 mL/min | 667 mg | Every 8 hours on Days 1 to 8
SAB | 30 to less than 50 mL/min | 667 mg | Every 12 hours from Day 9
SAB | 15 to less than 30 mL/min | 333 mg | Every 8 hours on Days 1 to 8
SAB | 15 to less than 30 mL/min | 333 mg | Every 12 hours from Day 9
SAB | Less than 15 mL/min, including hemodialysis [Administer ZEVTERA after intermittent hemodialysis on hemodialysis days, because ceftobiprole is removed by hemodialysis.] | 333 mg | Every 24 hours
ABSSSI or CABP | 30 to less than 50 | 667 mg | Every 12 hours
ABSSSI or CABP | 15 to less than 30 | 333 mg | Every 12 hours
ABSSSI or CABP | Less than 15 mL/min, including hemodialysis | 333 mg | Every 24 hours

2.4 Recommended Dosage Regimen for CABP in Pediatric Patients (2 Years to Less than 18 Years Old) with Renal Impairment

The recommended dosage of ZEVTERA in pediatric patients (2 years to less than 18 years old) with renal impairment (with eGFR less than 50 mL/min/1.73 m^2 and greater than or equal to 15 mL/min/1.73 m^2) is shown in Table 4. The duration of treatment for CABP in pediatric patients (2 years to less than 18 years old) with renal impairment is 7 days to 14 days.

Administer each prepared intravenous infusion solution of ZEVTERA over 2 hours at a concentration of 2.67 mg/mL for patients 12 years to less than 18 years old and at a concentration of 5.33 mg/mL for patients 2 years to less than 12 years old.

There is insufficient information to recommend dosage adjustments in pediatric patients 2 years of age and older with an eGFR less than 15 mL/min/1.73m^2.

There is insufficient information to recommend dosage adjustments in pediatric patients less than 2 years of age with any degree of renal impairment.

Table 4: ZEVTERA Recommended Dosage Regimens for Pediatric Patients (2 Years to less than 18 Years Old) with CABP and with Renal Impairment
Pediatric Age Group [Duration of treatment for CABP in pediatric patients (2 years to less than 18 years old) and with renal impairment is 7 days to 14 days.] | eGFR (mL/min/1.73 m^2) [Calculate using a validated GFR estimating equation for the approved age of the pediatric population.] | Dosage Regimen [667 mg ceftobiprole medocaril sodium is equivalent to 500 mg of ceftobiprole; 333 mg ceftobiprole medocaril sodium is equivalent to 250 mg of ceftobiprole; 10 mg/kg of ceftobiprole medocaril sodium is equivalent to 7.5 mg/kg of ceftobiprole; 13.3 mg/kg ceftobiprole medocaril sodium is equivalent to 10 mg/kg of ceftobiprole.]
12 years to less than 18 years old | 30 to less than 50 | 10 mg/kg (up to 667 mg) [Administer each prepared intravenous infusion solution of ZEVTERA over 2 hours at a concentration of 2.67 mg/mL for pediatric patients 12 years to less than 18 years old [see Dosage and Administration (2.5)].] every 12 hours
12 years to less than 18 years old | 15 to less than 30 | 10 mg/kg (up to 333 mg) every 12 hours
6 years to less than 12 years old | 30 to less than 50 | 10 mg/kg (up to 667 mg) [Administer each prepared intravenous infusion solution of ZEVTERA over 2 hours at a concentration of 5.33 mg/mL for pediatric patients 2 years to less than 12 years old [see Dosage and Administration (2.5)].] every 12 hours
6 years to less than 12 years old | 15 to less than 30 | 10 mg/kg (up to 333 mg) every 24 hours
2 years to less than 6 years old | 30 to less than 50 | 13.3 mg/kg every 12 hours (up to 667 mg)
2 years to less than 6 years old | 15 to less than 30 | 13.3 mg/kg every 24 hours (up to 333 mg)

2.5 Preparation of ZEVTERA Infusion Solution

ZEVTERA must first be reconstituted in the vial and then further diluted prior to administration by intravenous infusion over a period of 2 hours. Aseptic technique must be followed in preparing the infusion solution. See additional instructions for reconstitution and dilution below.

Parenteral drug products should be inspected visually for particulate matter and discoloration prior to administration, whenever solution and container permit. The solution for infusion should be clear to slightly opalescent and yellowish in color. Discard if discoloration or visible particles are observed.

Reconstitution of ZEVTERA in the Vial

- For adult and pediatric patients 12 years of age and older, reconstitute ZEVTERA lyophilized powder in the vial with 10 mL of sterile water for injection or 10 mL of 5% dextrose injection.
- For pediatric patients aged 3 months to less than 12 years old, ZEVTERA lyophilized powder must be reconstituted with 10 mL of 5% dextrose injection.
- After reconstitution, shake the reconstituted ZEVTERA vial vigorously until dissolution is completed, which in some cases may take up to 10 minutes. The volume of the resulting reconstituted solution is approximately 10.6 mL.
- Allow any foam formed to dissipate and then inspect the reconstituted solution visually to ensure the product is in solution and particulate matter is absent.
- The reconstituted solution contains 66.7 mg/mL of ceftobiprole medocaril sodium and must be further diluted using aseptic technique with the appropriate diluent as described below, prior to administration. If it is not possible to dilute the reconstituted solution immediately, the reconstituted solution may be stored refrigerated for up to 24 hours, and at room temperature for up to 1 hour. Discard any unused reconstituted solution [see Dosage and Administration (2.6)].

Dilution of Reconstituted ZEVTERA Solution and Administration of the Diluted Product

After reconstitution with the appropriate diluent, further dilute the reconstituted ZEVETRA solution, using aseptic technique with the appropriate diluent, to the appropriate volume of ZEVTERA infusion solution as described in Table 5.

Table 5: Preparation of Diluted ZEVTERA Solution for Infusion
Patient Age Group | Volume of diluent to be added to the vial | Volume of reconstituted solution to be withdrawn from the vial | Volume of Infusion solution to be administered [Gently invert 5-10 times to form a homogenous solution. Avoid vigorous agitation to prevent foaming.] | Concentration and final volume of the diluted product
Adult (18 years of age and older) | 10 mL | 10 mL | 250 mL 0.9% sodium chloride or 5% dextrose injection | 2.67 mg/mL in a 250 mL infusion bag (667 mg/250 mL)
Adult patients with renal Impairment (CLCR less than 30 mL/min) | 10 mL | 5 mL | 125 mL 0.9% sodium chloride or 5% dextrose injection | 2.67 mg/mL in a 125 mL infusion bag (333 mg/125 mL)
Pediatric Patients 12 Years of Age to Less than 18 Years of Age | 10 mL | Refer to Table 2 for the dose to determine volume of reconstituted solution needed according to weight-based dosing | The final volume to be administered should be calculated based on the patient body weight and must not exceed a maximum of 250 mL of 0.9% sodium chloride or 5% dextrose injection (do not exceed maximum of 667 mg/250 mL dose at a concentration of 2.67 mg/mL)
Pediatric Patients 12 Years of Age to Less than 18 Years of Age with renal Impairment | 10 mL | Renal Impairment: Refer to Table 4 for the dose to determine volume of reconstituted solution needed according to weight-based dosing | The final volume to be administered should be calculated based on the patient body weight and must not exceed a maximum of 250 mL of 0.9% sodium chloride or 5% dextrose injection (do not exceed maximum of 667 mg/250 mL dose at a concentration of 2.67 mg/mL)
Pediatric Patients 3 months to Less than 12 Years of Age | 10 mL | Refer to Table 2 for the dose to determine the volume of reconstituted solution needed according to weight-based dosing [For administration via infusion bags, bottles, or syringes: For example, for a dose equal to 667 mg, withdraw 10 mL of the reconstituted solution from the vial and inject into a suitable container of 125 mL of infusion solution.] , [For administration via a 50 mL syringe if the calculated dose does not exceed 267 mg: For example, for a dose equal to 267 mg, withdraw 4 mL of the reconstituted solution from the vial and withdraw 46 mL of the appropriate infusion solution into the syringe for infusion.] | The final volume to be administered should be calculated based on the patient body weight and must not exceed a maximum of 125 mL of 5% dextrose injection (do not exceed maximum of 667 mg/125 mL at a concentration of 5.33 mg/mL)
Pediatric Patients 2 years to less than 12 years of age with renal impairment | 10 mL | Renal Impairment: Refer to Table 4 for the dose to determine the volume of reconstituted solution needed according to weight-based dosing, | The final volume to be administered should be calculated based on the patient body weight and must not exceed a maximum of 125 mL of 5% dextrose injection (do not exceed maximum of 667 mg/125 mL at a concentration of 5.33 mg/mL)

2.6 Storage of Reconstituted and Diluted Infusion Solutions

Storage of Reconstituted ZEVTERA Solution in Vials

Upon reconstitution with the appropriate diluent, the reconstituted ZEVTERA solution in the vial should be transferred and diluted into the appropriate container. If it is not possible to dilute the reconstituted ZEVTERA solution immediately, the reconstituted solution may be stored refrigerated for up to 24 hours, and at room temperature for up to 1 hour. Discard any unused reconstituted solution.

Storage of Diluted ZEVTERA Solution in Infusion Bags

ZEVTERA solutions for infusions can be stored at room temperature or refrigerated at 2 °C to 8 °C. If the infusion solution is stored in the refrigerator, it should be equilibrated to room temperature prior to administration. ZEVTERA solutions should not be exposed to direct sunlight. The infusion solution does not need to be protected from light during administration. Do not freeze ZEVTERA solutions for infusions.

Storage for diluted ZEVTERA infusion solutions at a concentration of 2.67 mg/mL and 5.33 mg/mL for varying storage conditions are described in Tables 6 and 7.

Table 6: Storage Time for Diluted ZEVTERA Infusion Solutions for Adult and Pediatric Patients 12 Years to Less than 18 Years Old (2.67 mg/mL)
Reconstitution solution diluent (vial) | Infusion solution diluent | Infusion solutions stored at 25 °C NOT protected from light | Infusion solutions stored at 2 °C to 8 °C Protected from light
5% Dextrose solution for injection | 5% Dextrose solution for injection | 6 hours | 94 hours
5% Dextrose solution for injection | 0.9% Sodium chloride solution for injection | 4 hours | 24 hours
Sterile water for injection | 5% Dextrose solution for injection or 0.9% Sodium chloride solution for injection | 6 hours | 94 hours

Table 7: Storage Time for Diluted ZEVTERA Infusion Solutions for Pediatric Patients Less than 12 Years Old (5.33 mg/mL)
Reconstitution solution diluent (vial) | Infusion solution diluent | Infusion solutions stored at 25 °C NOT protected from light | Infusion solutions stored at 2 °C to 8 °C Protected from light
5% Dextrose solution for injection | 5% Dextrose solution for injection | 6 hours | 24 hours

2.7 Drug Compatibilities and Incompatibilities

ZEVTERA is compatible with 5% dextrose injection and 0.9 % sodium chloride injection [see Dosage and Administration (2.5)]. The compatibility of ZEVTERA with other drugs and infusion solutions other than 5% dextrose Injection or 0.9% sodium chloride Injection, has not been established.

ZEVTERA must not be mixed or administered simultaneously with calcium-containing solutions. Do not mix ZEVTERA with, or co-administer through, the same intravenous line or cannula with other drug products.

3 DOSAGE FORMS AND STRENGTHS

ZEVTERA (ceftobiprole medocaril sodium for injection) is available in a single-dose vial as a white, yellowish to slightly brownish, cake to broken cake or powder containing 667 mg of ceftobiprole medocaril sodium (equivalent to 500 mg of ceftobiprole) for reconstitution.

4 CONTRAINDICATIONS

ZEVTERA is contraindicated in patients with a known history of severe hypersensitivity to ZEVTERA, or to other members of the cephalosporin class [see Warnings and Precautions (5.2)].

5 WARNINGS AND PRECAUTIONS

5.1 Increased Mortality with Unapproved Use in Ventilator-Associated Bacterial Pneumonia Patients

In Trial 4, an increase in mortality was seen in the subgroup of patients with ventilator-associated bacterial pneumonia (VABP) who were treated with ZEVTERA (35/103 [34%] versus 24/102 [24%] in comparator-treated patients) [see Adverse Reactions (6.1)]. The cause of this increased mortality has not been established. Generally, deaths were associated with complications of infection or underlying co-morbidities. The safety and effectiveness of ZEVTERA for the treatment of VABP has not been established and the use of ZEVTERA for VABP is not approved.

5.2 Hypersensitivity Reactions

Serious hypersensitivity reactions, including anaphylaxis, were observed in ZEVTERA-treated patients in clinical trials [see Adverse Reactions (6.1)]. Serious and occasionally fatal hypersensitivity reactions and serious skin reactions have been reported in patients receiving beta-lactam antibacterial drugs.

Before therapy with ZEVTERA is instituted, careful inquiry about previous hypersensitivity reactions to other cephalosporins, penicillins, or other beta-lactam antibacterial drugs should be made. Maintain clinical supervision if this product is to be given to a penicillin- or other beta-lactam-allergic patient, because cross sensitivity among beta-lactam antibacterial agents has been established. Discontinue ZEVTERA if a hypersensitivity reaction occurs, and institute appropriate treatment.

5.3 Seizures and Other Central Nervous System Reactions

Seizures and other adverse central nervous system (CNS) reactions have been reported during treatment with ZEVTERA and other cephalosporins [see Adverse Reactions (6.1)].

Nonconvulsive status epilepticus (NCSE), encephalopathy, coma, asterixis, neuromuscular excitability, and myoclonia have been reported with cephalosporins particularly in patients with a history of epilepsy or when recommended dosages of cephalosporins were exceeded due to renal impairment. Adjust ZEVTERA dosing based on creatinine clearance [see Dosage and Administration (2.3, 2.4)].

Anticonvulsant therapy should be continued in patients with known seizure disorders. If CNS adverse reactions, including seizures, occur, patients should undergo a neurological evaluation to determine whether ZEVTERA should be discontinued.

5.4 Clostridioides difficile-Associated Diarrhea

Clostridioides difficile-associated diarrhea (CDAD) has been reported for nearly all systemic antibacterial agents, including ZEVTERA, and may range in severity from mild diarrhea to fatal colitis. Treatment with antibacterial agents alters the normal flora of the colon and may permit overgrowth of C. difficile.

C. difficile produces toxins A and B which contribute to the development of CDAD. Hypertoxin-producing strains of C. difficile cause increased morbidity and mortality, as these infections can be refractory to antibacterial therapy and may require colectomy. CDAD must be considered in all patients who present with diarrhea following antibacterial use. Careful medical history is necessary because CDAD has been reported to occur more than 2 months after the administration of antibacterial agents.

If CDAD is suspected or confirmed, ongoing antibacterial use not directed against C. difficile should be discontinued, if possible. Manage fluid and electrolyte levels as appropriate, supplement protein intake, monitor antibacterial treatment of C. difficile, and institute surgical evaluation as clinically indicated.

5.5 Development of Drug-Resistant Bacteria

Prescribing ZEVTERA in the absence of a proven or strongly suspected bacterial infection or a prophylactic indication is unlikely to provide benefit to the patient and increases the risk of the development of drug-resistant bacteria.

6 ADVERSE REACTIONS

The following adverse reactions are discussed in greater detail in the Warnings and Precautions section:

- Increased Mortality in Ventilator-Associated Bacterial Pneumonia Patients [see Warnings and Precautions (5.1)]
- Hypersensitivity Reactions [see Contraindications (4) and Warning and Precautions (5.2)]
- Seizures and Other Central Nervous System Reactions [see Warnings and Precautions (5.3)]
- Clostridioides difficile-Associated Diarrhea [see Warnings and Precautions (5.4)]

6.1 Clinical Trials Experience

Because clinical trials are conducted under widely varying conditions, adverse reaction rates observed in the clinical trials of a drug cannot be directly compared to rates in the clinical trials of another drug and may not reflect the rates observed in practice.

The safety of ZEVTERA was evaluated in adults in four controlled comparative phase 3 clinical trials (Trials 1 through 4) which included 1221 patients treated with ZEVTERA 667 mg (equivalent to 500 mg of ceftobiprole) administered by IV infusion over 2 hours every 6 to 8 hours and 1248 patients treated with comparator for a treatment period up to 42 days. The median age of patients treated with ZEVTERA was 56 years, ranging between 18 and 95 years old. Patients treated with ZEVTERA were predominantly male (64%) and White (82%).

The safety of ZEVTERA was also evaluated in pediatric patients aged 3 months to less than 18 years in a controlled phase 3 clinical trial (Trial 5) which included 138 patients with CABP and hospital-acquired bacterial pneumonia (HABP) requiring hospitalization. Although HABP was included in the safety data, the safety and effectiveness of ZEVTERA for the treatment of HABP has not been established and ZEVTERA is not approved for the treatment of HABP.

Adult Patients with Staphylococcus aureus Bloodstream Infection (Bacteremia)

ZEVTERA was evaluated in an active-controlled randomized, double-blind, multicenter phase 3 trial (Trial 1) in patients with Staphylococcus aureus bloodstream infection (bacteremia) (SAB) including right-sided infective endocarditis [see Clinical Studies (14.1)]. In Trial 1, 191 patients received ZEVTERA 667 mg (equivalent to 500 mg of ceftobiprole) administered as a 2-hour IV infusion every 6 hours from Day 1 to Day 8, and ZEVTERA 667 mg every 8 hours from Day 9 onwards, and 198 patients were treated with a comparator (daptomycin administered as an IV 0.5 hour infusion, 6 mg/kg up to 10 mg/kg every 24 hours, with optional aztreonam). The dose of study drugs were adjusted based on renal function.

The median age of patients treated with ZEVTERA was 57 years, ranging between 20-89 years old with approximately 30% aged greater than or equal to 65 years. Patients treated with ZEVTERA were predominantly male (68%), White (95%), and from Europe (93%). The median duration of treatment was 21 days in both treatment arms.

Serious Adverse Reactions and Adverse Reactions Leading to Discontinuation

In Trial 1, a total of 36/191 (18.8%) patients with SAB treated with ZEVTERA and 45/198 (22.7%) of patients with SAB treated with daptomycin ± aztreonam experienced serious adverse reactions. Discontinuation of treatment due to any adverse reaction occurred in 18/191 (9.4%) of patients treated with ZEVTERA, and 18/198 (9.1%) of patients treated with daptomycin ± aztreonam. In patients treated with ZEVTERA, the most common adverse reactions leading to discontinuation were nausea, vomiting, rash, and urticaria, each occurring in 2/191 (1%). Deaths occurred in 17/191 (8.9%) patients treated with ZEVTERA and 18/198 (9.1%) patients treated with daptomycin ± aztreonam.

Common Adverse Reactions

Table 8 lists the most common adverse reactions occurring in ≥ 2% of SAB adult patients receiving ZEVTERA in Trial 1.

Table 8: Selected Adverse Reactions Occurring in ≥ 2% of SAB Adult Patients Receiving ZEVTERA in Trial 1 [Trial 1 was not designed to evaluate meaningful comparisons of the incidence of adverse reactions in the ZEVTERA and the daptomycin plus or minus aztreonam treatment groups.]
Adverse Reaction | ZEVTERA [ZEVTERA 667 mg IV over 2-hours every 6 hours from Day 1 to Day 8, and every 8 hours from Day 9 onwards, with dosing adjustment based on renal function. 667 mg ceftobiprole medocaril sodium is equivalent to 500 mg of ceftobiprole.] N = 191 | Daptomycin [Daptomycin 6 mg/kg up to 10 mg/kg IV over 0.5 hour every 24 hours, with dosing adjustment based on renal function.] ± Aztreonam N = 198
Anemia [Anemia includes the following terms: anemia, hemoglobin decreased, hypochromic anemia, and normochromic normocytic anemia.] | 12% | 13%
Nausea | 10% | 4%
Hypokalemia [Hypokalemia replaces the term blood potassium decreased.] | 9% | 3%
Vomiting | 8% | 2%
Hepatic enzyme and bilirubin increased [Hepatic enzyme increased includes the following terms: alanine aminotransferase increased, aspartate aminotransferase increased, blood alkaline phosphatase increased, gamma-glutamyltransferase increased, blood bilirubin increased, and hyperbilirubinemia.] | 8% | 10%
Diarrhea | 7% | 3%
Blood creatinine increased [Blood creatinine increased includes the following terms: acute kidney injury, blood creatinine increased, creatinine renal clearance decreased, oliguria, and renal impairment.] | 7% | 5%
Hypertension [Hypertension includes the following terms: hypertension, blood pressure increased, and hypertensive crisis.] | 5% | 2%
Leukopenia [Leukopenia includes the following terms: leukopenia, lymphocyte count decreased, lymphopenia, neutropenia, neutrophil count decreased, and white blood cell count decreased.] | 4% | 3%
Pyrexia [Pyrexia includes the following terms: hyperthermia and pyrexia.] | 4% | 3%
Abdominal pain [Abdominal pain includes the following terms: abdominal pain upper and abdominal tenderness.] | 3% | 1%
Fungal infection [Fungal infection includes the following terms: candida infection, candida sepsis, fungal test positive, oral candidiasis, vulvovaginal candidiasis, and tinea pedis.] | 3% | 2%
Headache | 3% | 3%
Dyspnea [Dyspnea includes the following terms: dyspnea and respiratory distress.] | 2% | 1%
SAB = Staphylococcus aureus bacteremia.

Adult Patients with Acute Bacterial Skin And Skin Structure Infections

ZEVTERA was evaluated in an active-controlled, randomized, double-blind, multicenter phase 3 trial (Trial 2) in patients with acute bacterial skin and skin structure infections (ABSSSI) [see Clinical Studies (14.2)].

In Trial 2, 334 patients received ZEVTERA 667 mg (equivalent to 500 mg of ceftobiprole) administered as a 2-hour IV infusion every 8 hours, and 342 patients were treated with vancomycin plus aztreonam. The daily dose of vancomycin was 2 grams, as a 1 gram fixed dose or 15 mg/kg, administered as a 2-hour IV infusion every 12 hours. Aztreonam was administered as a 1 gram fixed dose as a 0.5-hour IV infusion every 12 hours and the requirement for aztreonam therapy was reassessed at the 72-hour study visit. The dose of study drugs was adjusted based on renal function.

The median age of patients treated with ZEVTERA was 51 years ranging from 18–89 years old with approximately 12% aged greater than or equal to 65 years. Patients treated with ZEVTERA were mostly male (59%), White (95%), and from the United States (60%). Patients across treatment arms received treatment for a median duration of 6 days.

Serious Adverse Reactions and Adverse Reactions Leading to Discontinuation

In Trial 2, a total of 6/334 (1.8%) ABSSSI patients treated with ZEVTERA and 12/342 (3.5%) of ABSSSI patients treated with vancomycin plus aztreonam experienced serious adverse reactions. Discontinuation of treatment due to any adverse reaction occurred in 6/334 (1.8%) of patients treated with ZEVTERA, and 10/342 (2.9%) of patients treated with vancomycin plus aztreonam. In patients treated with ZEVTERA, the most common adverse reactions leading to discontinuation were dysgeusia and both pruritus and rash, occurring in 1/334 (0.3%). Deaths occurred in 1/334 (0.3%) patients treated with ZEVTERA and 2/342 (0.6%) patients treated with vancomycin plus aztreonam.

Common Adverse Reactions

Table 9 lists the most common adverse reactions occurring in ≥ 2% of ABSSSI patients receiving ZEVTERA in Trial 2.

Table 9: Selected Adverse Reactions Occurring in ≥ 2% of ABSSSI Adult Patients Receiving ZEVTERA in Trial 2 [Trial 2 was not designed to evaluate meaningful comparisons of the incidence of adverse reactions in the ZEVTERA and the vancomycin plus or minus aztreonam treatment groups.]
Adverse Reaction | ZEVTERA [ZEVTERA 667 mg IV over 2-hours every 8 hours with dosing adjustment based on renal function. 667 mg ceftobiprole medocaril sodium is equivalent to 500 mg of ceftobiprole.] N = 334 | Vancomycin plus Aztreonam [Vancomycin IV, as fixed 1 gram or 15 mg/kg, administered over 2 hours every 12 hours with dosing adjustment based on renal function; aztreonam IV 1 gram over 0.5 hour every 12 hours with dosing adjustment based on renal function.] N = 342
Nausea | 11% | 6%
Diarrhea | 6% | 5%
Headache | 6% | 7%
Injection site reaction [Infusion site reaction includes the following terms: injection site reaction and infusion-related reaction.] | 2% | 3%
Hepatic enzyme increased [Hepatic enzyme increased includes the following terms: alanine aminotransferase increased, aspartate aminotransferase increased, blood alkaline phosphatase increased, and gamma-glutamyltransferase increased.] | 2% | 3%
Rash [Rash includes the following terms: rash, drug eruption, and dermatitis.] | 2% | 3%
Vomiting | 2% | 2%
Dysgeusia | 2% | 0%
ABSSSI = Acute Bacterial Skin and Skin Structure Infections.

Adult Patients with Community-Acquired Bacterial Pneumonia

ZEVTERA was evaluated in an active-controlled, randomized, double-blind, multicenter phase 3 study in adult patients with community-acquired bacterial pneumonia (CABP) [see Clinical Studies (14.3)].

In Trial 3, 310 patients received ZEVTERA 667 mg (equivalent to 500 mg of ceftobiprole) every 8 hours as a 2-hour IV infusion, and 322 patients were treated with ceftriaxone 2 grams as a 0.5 hour IV infusion with or without linezolid 600 mg every 12 hours as a 60-minute IV infusion. The dose of ZEVTERA was adjusted based on renal function.

The median age of patients treated with ZEVTERA was 56 years, ranging from 18–90 with approximately 36% aged greater than or equal to 65 years. Approximately 62% of patients were White, 45% were from outside Europe or the United States, and 57% were male. Patients across treatment arms received treatment for a median duration of 9 days.

Serious Adverse Reactions and Adverse Reactions Leading to Discontinuation

In Trial 3, a total of 35/310 (11.3%) patients with CABP treated with ZEVTERA and 37/322 (11.5%) patients with CABP treated with ceftriaxone ± linezolid experienced serious adverse reactions. Discontinuation of treatment due to any adverse reaction occurred in 18/310 (5.8%) of patients treated with ZEVTERA, and 12/322 (3.7%) of patients treated with ceftriaxone ± linezolid. The most common adverse reaction leading to discontinuation in patients treated with ZEVTERA was vomiting, occurring in 4/310 (1.3%). Deaths occurred in 9/310 (2.9%) patients treated with ZEVTERA and 9/322 (2.8%) in patients treated with ceftriaxone ± linezolid.

Common Adverse Reactions

Table 10 lists the most common adverse reactions occurring in ≥ 2% of CABP adult patients receiving ZEVTERA in Trial 3.

Table 10: Selected Adverse Reactions Occurring in ≥ 2% of CABP Adult Patients Receiving ZEVTERA in Safety Analysis Set in Trial 3
Adverse Reaction | ZEVTERA [ZEVTERA 667 mg IV over 2-hours every 8 hours with dosing adjustment based on renal function. 667 mg ceftobiprole medocaril sodium is equivalent to 500 mg of ceftobiprole.] N = 310 | Ceftriaxone [Ceftriaxone 2 grams IV over 0.5 hour every 24 hours, with or without linezolid 600 mg IV over 1 hour every 12 hours.] ± linezolid N = 322
Nausea | 10% | 4%
Hepatic enzyme increased [Hepatic enzyme increased includes the following terms: aspartate aminotransferase increased, gamma-glutamyltransferase increased, blood alkaline phosphatase increased, alanine aminotransferase increased, hepatic enzyme increased, transaminases increased, alanine aminotransferase, and liver function test increased.] | 10% | 11%
Vomiting | 9% | 3%
Diarrhea | 7% | 9%
Headache | 7% | 7%
Rash [Rash includes the following terms: dermatitis contact, dermatitis allergic, rash, and rash pruritic.] | 5% | 2%
Insomnia | 5% | 4%
Abdominal pain [Abdominal pain includes the following terms: abdominal discomfort, abdominal pain, and abdominal pain upper.] | 4% | 3%
Phlebitis [Phlebitis includes the following terms: phlebitis, and injection site phlebitis.] | 4% | 2%
Hypertension [Hypertension includes the following terms: hypertension, blood pressure increased, and hypertensive crisis.] | 4% | 4%
Dizziness | 3% | 2%
CABP = Community-Acquired Bacterial Pneumonia.

Adult Patients with Unapproved Use of Hospital-Acquired Bacterial Pneumonia and Ventilator-Associated Bacterial Pneumonia

ZEVTERA was evaluated in an active-controlled, randomized, double-blind, multicenter, phase 3 trial (Trial 4) in patients with hospital-acquired bacterial pneumonia/ventilator-associated bacterial pneumonia (HABP/VABP) . Although HABP/VABP are included in the safety data, the safety and effectiveness of ZEVTERA for the treatment of HABP/VABP have not been established and ZEVTERA is not approved for HABP or VABP.

In Trial 4, 386 patients received ZEVTERA 667 mg (equivalent to 500 mg of ceftobiprole) every 8 hours as a 2-hour IV infusion, and 386 patients were treated with ceftazidime 2 grams every 8 hours as a 2-hour IV infusion with or without linezolid 600 mg every 12 hours as a 1-hr infusion. The dose of ZEVTERA and ceftazidime were adjusted based on renal function.

The median age of patients treated with ZEVTERA was 62.5 years (range 18 - 95) with approximately 47% aged 65 years or older. Approximately 81% of the patients were White, most were outside of the United States (88%) and 72% were male. Patients across treatment arms received treatment for a median duration of 8 days.

Serious Adverse Reactions and Adverse Reactions Leading to Discontinuation

In Trial 4, a total of 140/386 (36.3%) HABP/VABP adult patients treated with ZEVTERA and 123/386 (31.9%) HABP/VABP adult patients treated with ceftazidime ± linezolid experienced serious adverse reactions. Discontinuation of treatment due to any adverse reaction occurred in 54/386 (14%) of patients treated with ZEVTERA, and 40/386 (10.4%) of patients treated with ceftazidime ± linezolid. Deaths occurred in 88/386 patients (22.8%) treated with ZEVTERA and 84/386 patients (21.8%) treated with ceftazidime ± linezolid. In the subgroup of patients with VABP, 35/103 patients treated with ZEVTERA died (34.0%) versus 24/102 (23.5%) of the patients treated with ceftazidime ± linezolid. In the subgroup of patients with HABP, 53/283 patients treated with ZEVTERA died (18.7%) versus 60/284 patients treated with ceftazidime ± linezolid (21.1%).

Common Adverse Reactions

Common adverse reactions occurring in >2% of HABP/VABP adult patients who received ceftobiprole in Trial 4 include diarrhea, hypokalemia, hyponatremia, hepatic enzyme increased, vomiting, anemia, rash, phlebitis, nausea, abdominal pain, and seizures.

Adverse Reactions Reported in <2% of Adults Treated with ZEVTERA

The following adverse reactions were reported in ZEVTERA-treated adult patients at a rate of less than 2% in Trials 1, 2, 3, and 4:

Blood and lymphatic system disorders: | Thrombocytosis, Thrombocytopenia
Gastrointestinal disorders: | Dyspepsia, Dysphagia
General disorders and administration site conditions: | Fatigue, Chills, Facial swelling, Infusion site pain
Immune system disorders: | Hypersensitivity, Angioedema, Anaphylactic shock
Infections and infestations: | Mucocutaneous fungal infections
Investigations: | Blood lactate dehydrogenase increased, Blood triglycerides increased, Prothrombin time prolonged
Psychiatric disorders: | Anxiety, Irritability
Renal and urinary disorders: | Pollakiuria
Respiratory, thoracic and mediastinal disorders: | Bronchospasm, Wheezing
Skin and subcutaneous tissue disorders: | Pruritus
Vascular disorders: | Thrombosis

Pediatric Patients with Community-Acquired Bacterial Pneumonia

ZEVTERA was evaluated in an active-controlled, randomized, investigator-blinded, multicenter phase 3 study (Trial 5) in pediatric patients aged 3 months to less than 18 years with HABP or CABP requiring hospitalization. Although patients with HABP are included in the safety data, the safety and effectiveness of ZEVTERA for the treatment of HABP has not been established and ZEVTERA is not approved for HABP.

In Trial 5, 94 patients received ZEVTERA 13.3 mg/kg (equivalent to 10 mg/kg of ceftobiprole) to 26.7 mg/kg (equivalent to 20 mg/kg of ceftobiprole – higher than the recommended approved dose) [see Dosage and Administration (2.2, 2.4)]. ZEVTERA was administered by intravenous infusion every 8 hours, age-adjusted for dose and infusion duration (2-hour or 4-hour infusion). In the comparator arm, 44 patients received either ceftriaxone 50-80 mg/kg IV as a single daily dose (maximum 2 grams/day) for CABP or ceftazidime 50 mg/kg IV every 8 hours (maximum 6 grams/day) for HABP, with or without vancomycin 10-15 mg/kg IV every 6 hours (maximum 2 grams/day). The median age of study patients was 5 years, ranging from 0.6 to 17 years. All patients were from Europe, 100% were classified as White and 56% of patients were male.

Serious Adverse Reactions and Adverse Reactions Leading to Discontinuation

In Trial 5, a total of 7/94 (7.4%) pediatric patients treated with ZEVTERA and 2/44 (4.5%) patients in the comparator group experienced serious adverse reactions. Discontinuation of treatment due to any adverse reaction occurred in 4/94 (4.3%) of patients treated with ZEVTERA and 0/44 patients treated in the comparator group. Adverse reactions leading to treatment discontinuation in patients who received ZEVTERA included aggravated pneumonia, pleuritis, urticaria, and hypersensitivity, each occurring in 1/94 (1.1%). There were no deaths in either arm of the pediatric study.

The most common adverse reactions, occurring in ≥ 2% of pediatric patients treated with ZEVTERA were vomiting (7.4%), headache (3.2%), hepatic enzyme increased (including alanine aminotransferase increased and aspartate aminotransferase increased) (3.2%), diarrhea, infusion site reaction, phlebitis, and pyrexia (all 2.1%).

6.2 Postmarketing Experience

The following adverse reactions and altered laboratory tests have been identified during post-approval use of ZEVTERA and ceftobiprole outside of the United States, or other cephalosporin-class antibacterial drugs. Because these reactions are reported voluntarily from a population of uncertain size, it is not always possible to reliably estimate their frequency or establish a causal relationship to drug exposure.

Altered Laboratory Tests: Positive direct Coombs' test, false-positive test for urinary glucose.
Blood and lymphatic system disorders: Agranulocytosis, aplastic anemia.
Hepatobiliary disorders: Hepatic dysfunction including cholestasis.
Immune system disorders: Drug fever, serum sickness-like reaction.
Nervous system disorders: Myoclonus.
Renal and urinary disorders: Renal dysfunction, toxic nephropathy.
Vascular disorders: Hemorrhage, hypertension.

7 DRUG INTERACTIONS

7.1 Organic Anion Transporting Polypeptide 1B1/1B3 (OATP1B1/OATP1B3) Substrates

ZEVTERA may increase the plasma concentrations of OATP1B1 and OATP1B3 substrates. Concomitant administration is not recommended [see Clinical Pharmacology (12.3)].

7.2 Drug-Laboratory Test Interactions

Dipstick Tests

ZEVTERA may result in false-positive results in dipstick tests (urine protein, ketones, or occult blood). Use alternate clinical laboratory methods of testing to confirm positive tests.

Serological Testing

Treatment with ZEVTERA has the potential to interfere with serological testing, such as the Coombs test. In clinical studies there was no evidence of hemolytic anemia in adults or children. However, the possibility that hemolytic anemia may occur cannot be ruled out. Patients experiencing anemia during or after treatment should be investigated for this possibility.

8 USE IN SPECIFIC POPULATIONS

8.1 Pregnancy

Risk Summary

There are no available data with use of ZEVTERA in pregnant women to evaluate for a drug-associated risk of major birth defects, miscarriage or other adverse maternal or fetal outcomes. Available data from published observational studies and case reports over several decades with cephalosporin use in pregnant women have not established drug-associated risks of major birth defects, miscarriage, or other adverse maternal or fetal outcomes. Available studies have methodologic limitations, including small sample size, retrospective data collection, and inconsistent comparator groups, and cannot definitively establish the absence of risk.

Intravenous administration of ceftobiprole medocaril to pregnant rats and monkeys during organogenesis showed no evidence of adverse fetal developmental outcomes at doses approximately 1.4 times and 0.9 times, respectively, the maximum recommended human dose (MRHD). Some evidence of maternal toxicity (slight reduction in body weight and food consumption) was noted in pregnant monkeys at 0.9 times the MRHD. Intravenous administration of ceftobiprole medocaril to rats 2-weeks prior to mating, during organogenesis, and through lactation resulted in no adverse fertility or fetal development effects in offspring at doses approximately 1.4 times the MRHD (see Data).

The background risk of major birth defects and miscarriage for the indicated population is unknown. All pregnancies have a background risk of birth defect, loss, or other adverse outcomes. In the U.S. general population, the estimated background risks of major birth defects and miscarriage in clinically recognized pregnancies is 2% to 4% and 15% to 20%, respectively.

Data

Animal Data

Pregnant rats administered ceftobiprole medocaril intravenously at doses up to 360 mg/kg/day (approximately 1.4 times the MRHD based on total body surface area (BSA)-normalized comparisons) during organogenesis on gestation days (GD) 6 to 17 showed no adverse fetal development effects. Maternal body weight gain and food consumption were slightly decreased at 360 mg/kg/day.

Pregnant cynomolgus monkeys were administered ceftobiprole medocaril intravenously at doses up to 120 mg/kg/day (approximately 0.9 times the MRHD based on BSA comparison) during organogenesis (GD 20 to 50). Maternal body weight gain and food consumption were slightly reduced at 120 mg/kg/day. This dose was associated with a slight increase in abortion rate (approximately 10% above historical controls). No other fetal development adverse effects (i.e., no fetal malformations) were observed at the high dose.

In a pre- and post-natal development toxicity study, ceftobiprole medocaril was administered intravenously to pregnant rats during organogenesis starting at GD 6 and continuing to lactation day 21 (L21) at doses up to 360 mg/kg (approximately 1.4 times the MRHD based on BSA comparisons). Maternal toxicity (mortality, reduced food consumption and body weight gain in surviving females during gestation) was observed at the high dose. Effects in the offspring were also observed at the high dose during the post-natal pre-weaning period (decrease in the number of pups born per litter and decreased post-natal survival up to day 4 after birth). No adverse effects were observed in surviving pups during the post-natal postweaning development period (days 5-22) at doses up to 360 mg/kg.

8.2 Lactation

Risk Summary

There are no data on the presence of ceftobiprole in human milk, the effects of ceftobiprole on the breastfed infant, or the effects of ceftobiprole on milk production. Animal studies have shown that ceftobiprole was excreted in milk of lactating rats at low concentrations (see Data). When a drug is present in animal milk, it is likely the drug will be present in human milk. The developmental and health benefits of breastfeeding should be considered along with the mother's clinical need for ZEVTERA and any potential adverse effects on the breastfed child from ZEVTERA or from the underlying maternal conditions.

Data

During pregnancy, rats were administered ceftobiprole at doses of 175, 250, and 360 mg/kg/day from 14-days pre-mating through lactation/postpartum day 21. Ceftobiprole was detected in the milk of lactating rats 2 hours post-dose on lactation day 20 at levels approximately 20% of the corresponding maternal plasma ceftobiprole levels. The concentration of ceftobiprole in animal milk does not necessarily predict the concentration of drug in human milk.

8.4 Pediatric Use

The safety and effectiveness of ZEVTERA have been established for the treatment of CABP in pediatric patients 3 months to less than 18 years. Use of ZEVTERA in this age group is supported by evidence from an adequate and well-controlled trial of ZEVTERA in adults, with additional pharmacokinetic, safety and efficacy data from pediatric trials [see Adverse Reactions (6.1), Clinical Pharmacology (12.3), Clinical Studies (14.3)].

The safety and effectiveness of ZEVTERA have not been established for the treatment of CABP in pediatric patients less than 3 months of age.

The safety and effectiveness of ZEVTERA have not been established for the treatment of ABSSSI and SAB in pediatric patients.

8.5 Geriatric Use

Of the 835 adult CABP, ABSSSI, and SAB patients treated with ZEVTERA in the Trials 1, 2 and 3, 210 patients (25%) were 65 years of age and older, including 85 patients (10%) 75 years of age and older. No overall differences in safety or effectiveness of ZEVTERA were observed between patients 65 years of age and older and younger adult patients.

No clinically significant changes in the pharmacokinetics of ZEVTERA were observed in patients 65 years of age and older compared to younger adult patients [see Clinical Pharmacology (12.3)]. Dosage adjustment for geriatric patients should be based on renal function [see Dosage and Administration (2.3), Use in Specific Populations (8.6) and Clinical Pharmacology (12.3)].

8.6 Renal Impairment

Adult Patients

The ZEVTERA dosage is reduced in adult patients with CLCR < 50 mL/min, including patients with a CLCR < 15 mL/min either receiving or not receiving hemodialysis [see Dosage and Administration (2.3)].

Renal impairment (CLCR < 50 mL/min) increases ceftobiprole AUC in adult patients [see Clinical Pharmacology (12.3)], which may increase the risk of ZEVTERA adverse reactions.

ZEVTERA is removed by hemodialysis; thus, ZEVTERA should be administered after intermittent hemodialysis on hemodialysis days [see Dosage and Administration (2.2) and Clinical Pharmacology (12.3)].

Pediatric Patients

The ZEVTERA dosage is reduced in pediatric patients 2 years to less than 18 years old with renal impairment (eGFR 15 to < 50 mL/min/1.73 m^2) [see Dosage and Administration (2.4)].

Use in pediatric patients 2 years to less than 18 years old with renal impairment (eGFR 15 to < 50 mL/min/1.73 m^2) is predicted to increase ceftobiprole AUC [see Clinical Pharmacology (12.3)], which may increase the risk of ZEVTERA adverse reactions. The effect of any degree of renal impairment in pediatric patients younger than 2 years of age or in pediatric patients 2 years to less than 18 years old with an eGFR < 15 mL/min/1.73 m^2 either receiving or not receiving hemodialysis on ceftobiprole pharmacokinetics is unknown.

Augmented Renal Clearance

Increase the ZEVTERA dosing frequency in adult patients with augmented renal clearance (CLCR > 150 mL/min).

Use in adult patients with augmented renal clearance (CLCR > 150 mL/min) is predicted to decrease ceftobiprole exposure [see Clinical Pharmacology (12.3)], which may reduce ZEVTERA efficacy. The effect of augmented renal clearance function (CLCR > 150 mL/min) on ZEVTERA pharmacokinetics in pediatric patients is unknown.

10 OVERDOSAGE

There is no information on clinical signs and symptoms associated with an overdose of ZEVTERA. For patients who receive doses greater than the recommended dosage regimen and have unexpected adverse reactions associated with ZEVTERA, discontinue ZEVTERA, treat symptomatically, and institute general supportive treatment.

ZEVTERA can be removed by hemodialysis. However, no information is available on the use of hemodialysis to treat overdose [see Clinical Pharmacology (12.3)].

11 DESCRIPTION

ZEVTERA (ceftobiprole medocaril sodium for injection) contains sodium salt of ceftobiprole medocaril, a semisynthetic, cephalosporin antibacterial, for intravenous use. Chemically, ceftobiprole medocaril is (6R,7R)-7-[[(2Z)-2-(5-amino-1,2,4-thiadiazol-3-yl)-2-hydroxyiminoacetyl]amino]-3-[(E)-[1-[(3R)-1-[(5-methyl-2-oxo-1,3-dioxol-4-yl)methoxycarbonyl]pyrrolidin-3-yl]-2-oxopyrrolidin-3-ylidene]methyl]-8-oxo-5-thia-1-azabicyclo[4.2.0]oct-2-ene-2-carboxylic acid. Its molecular weight is 690.6 g/mol. The empirical formula is C26H25N8NaO11S2.

Figure 1 Chemical Structure of ceftobiprole medocaril

ZEVTERA vials contain 667 mg of ceftobiprole medocaril sodium (equivalent to 500 mg of ceftobiprole). The powder for injection is a white, yellowish to slightly brownish sterile powder. Each vial includes inactive ingredient citric acid monohydrate (26.3 mg/vial) as a buffer component and sodium hydroxide (q.s.) as a pH adjustment agent. Each vial of ZEVTERA contains approximately 32 mg of sodium.

The pH of the reconstituted solution is 4.5–5.5.

12 CLINICAL PHARMACOLOGY

12.1 Mechanism of Action

ZEVTERA is an antibacterial drug [see Microbiology (12.4)]

12.2 Pharmacodynamics

Ceftobiprole exposure-response relationships and the time course of pharmacodynamic response are unknown.

Time Above the Minimum Inhibitory Concentration (MIC)

The time that the unbound plasma concentration of ceftobiprole exceeds the MIC of Staphylococcus aureus, Streptococcus pneumoniae, and species of Enterobacterales correlates with efficacy in a neutropenic murine thigh infection model [see Clinical Pharmacology (12.4)].

Cardiac Electrophysiology

At a dose 1 to 2 times the maximum recommended dose, ZEVTERA does not prolong the QT interval to any clinically relevant extent.

12.3 Pharmacokinetics

Ceftobiprole medocaril is the prodrug of the active moiety ceftobiprole. No clinically significant differences in the pharmacokinetics of ceftobiprole were observed with ZEVTERA following single or multiple dose administration. Ceftobiprole exhibits linear and time-independent pharmacokinetics. The Cmax and AUC increase proportionally with the dose over a range of 125 mg to 1000 mg (0.25 to 2 times the highest approved recommended adult dosage).

The mean pharmacokinetic parameters of ceftobiprole in healthy adults with normal renal function after single and multiple 2-hour IV infusions of ZEVTERA 667 mg (equivalent to 500 mg of ceftobiprole) administered every 8 hours are summarized in Table 11. Pharmacokinetic parameters were similar for single and multiple dose administrations.

Table 11: Mean (Standard Deviation) Pharmacokinetic Parameters of ZEVTERA in Healthy Adults
Parameter | Multiple doses administered every 8 hours as a 2-hour infusion (n = 27)
Cmax (µg/mL) | 33.0 (4.83)
AUC0-8h (µg•h/mL) | 102 (11.9)
Distribution
% Bound to human plasma protein | 16
% ELF/unbound plasma | 15-19
Vss (L) | 18
Metabolism (Minimally Metabolized)
t1/2 (h) | 3.3 (0.3)
CL (L/h) | 4.98 (0.582)
Excretion
Major route of elimination | Renal
% excreted unchanged in urine | 83
Cmax = Maximum plasma concentration; AUC0-8h = Area under the plasma concentration-time curve from 0 to 8 h; Vss = Volume of distribution at steady state; CL = Clearance.

Specific Populations

No clinically significant differences in the pharmacokinetics of ceftobiprole were observed in adults based on age (18 to 91 years), gender (36% female), or race/ethnicity (88% white, 3% Black, 5% Asian). The effect of hepatic impairment on ceftobiprole pharmacokinetics is unknown.

Patients with Renal Impairment

No clinically significant differences in the pharmacokinetics of ceftobiprole were observed in adult subjects and subjects with mild renal impairment (CLCR 50 to 80 mL/min). Ceftobiprole AUC increased 2.5-fold in adult subjects with moderate renal impairment (CLCR 30 to < 50 mL/min) and 3.3-fold in severe renal impairment (CLCR < 30 mL/min). The effect of any degree of renal impairment in pediatric patients less than 2 years of age or in pediatric patients with CLCR < 15 mL/min/1.73 m^2 on ceftobiprole pharmacokinetics is unknown.

End-stage Renal Disease Requiring Dialysis

No clinically significant difference in the pharmacokinetics of ceftobiprole were observed in adult patients with ESRD (CLCR < 15 mL/min) compared to healthy adult subjects based on limited PK data and pharmacokinetic modeling and simulation. Ceftobiprole was demonstrated to be removed by hemodialysis in patients receiving ZEVTERA.

Patients with Augmented Renal Clearance

A clinically significant reduction in ceftobiprole exposure is predicted in adult patients with augmented renal clearance (CLCR > 150 mL/min) based upon a mechanistic understanding of this drug. The effect of augmented renal clearance (CLCR > 150 mL/min) on ceftobiprole pharmacokinetics in pediatric patients is unknown.

Pediatric Use

No clinically significant differences in the pharmacokinetics of ceftobiprole were observed between pediatric patients from birth to < 18 years with normal renal function following administration of an intravenous dose of ZEVTERA. ZEVTERA is not approved for use in pediatric patients less than 3 months of age [see Use in Specific Populations (8.4)].

Drug Interaction Studies

In Vitro Studies

Ceftobiprole does not inhibit or induce CYP450 1A2, 2B6, 2C8, 2C9, 2C19, 2D6, or 3A4/5.

Transporter Systems

Ceftobiprole is an inhibitor of OATP1B1, OATP1B3, MRP2 and BSEP but is not an inhibitor of P-glycoprotein, BCRP, OAT1, OAT3, OCT1, OCT2, or MATE1.

12.4 Microbiology

Mechanism of Action

Ceftobiprole is a cephalosporin with bactericidal activity by inhibition of bacterial cell wall synthesis. Ceftobiprole has in vitro activity against gram-positive and gram-negative bacteria, including methicillin-resistant and susceptible Staphylococcus aureus. Bactericidal activity is mediated through binding to essential penicillin-binding proteins (PBPs) and inhibiting their transpeptidase activity, which is essential for the synthesis of the peptidoglycan layer of the bacterial cell wall. Ceftobiprole has a high affinity for S. aureus PBPs 1 – 4, including PBP2a in methicillin-resistant Staphylococcus aureus, and PBP2x and PBP2b in penicillin-resistant Streptococcus pneumoniae.

Resistance

Ceftobiprole is not active against gram-negative bacteria producing extended-spectrum β-lactamases (ESBLs) from the TEM, SHV or CTX-M families, serine carbapenemases (such as KPC), class B metallo-β-lactamases, class C (AmpC cephalosporinases) if expressed at high levels), and Ambler class D β-lactamases including carbapenemases.

No cross-resistance with other classes of antimicrobials has been identified. Although cross-resistance may occur, some isolates resistant to other cephalosporins may be susceptible to ceftobiprole.

Interaction with Other Antimicrobials

In vitro studies have not demonstrated any antagonism between ceftobiprole and other commonly-used antibacterial agents (e.g., gentamicin, vancomycin, daptomycin, rifampicin) against strains of Staphylococcus aureus. Against Escherchia coli, no antagonism was observed between ceftobiprole and doripenem or levofloxacin.

Activity against Bacteria in Animal Infection Models

Ceftobiprole demonstrated activity in a neutropenic murine thigh infection model reducing tissue counts of MRSA. Ceftobiprole was effective in treating experimental murine septicemia for strains of MSSA, MRSA, S. pneumoniae (including strains of penicillin-resistant S. pneumoniae [PRSP]), E. coli expressing TEM-1 and Act-1 AmpC cephalosporinase, K. pneumoniae, C. freundii, S. marcescens, and P. mirabilis. In an acute mouse model of pneumonia, ceftobiprole was effective against S. pneumoniae (ceftobiprole MICs < 0.5 µg/mL, including a strain of PRSP). In a rabbit model of meningitis, ceftobiprole was effective at clearing strains of E. coli, K. pneumoniae and β-lactamase positive and negative H. influenzae. In both a rat and rabbit model of endocarditis, ceftobiprole did not sterilize but was effective in reducing cardiac vegetations of MRSA including a vancomycin intermediate strain (ceftobiprole MIC ≤ 2 µg/mL). Similarly, in both a rat and rabbit model of osteomyelitis, ceftobiprole was effective in clearing MRSA infection (ceftobiprole MIC ≤ 1µg/mL). The clinical significance of the above findings in animal infection models is not known.

Antimicrobial Activity

ZEVTERA has been shown to be active against most isolates of the following bacteria, both in vitro and in clinical infections [see Indications and Usage (1)].

SAB

Gram-positive bacteria

Staphylococcus aureus (including methicillin-susceptible and methicillin-resistant isolates)

ABSSSI

Gram-positive bacteria

Staphylococcus aureus (including methicillin-susceptible and methicillin-resistant isolates)
Streptococcus pyogenes

Gram-negative bacteria

Klebsiella pneumoniae

CABP

Gram-positive bacteria

Staphylococcus aureus (including methicillin-susceptible isolates)
Streptococcus pneumoniae

Gram-negative bacteria

Escherichia coli
Klebsiella pneumoniae
Haemophilus influenzae
Haemophilus parainfluenzae

The following in vitro data are available, but their clinical significance is unknown. At least 90 percent of the following bacteria exhibit an in vitro minimum inhibitory concentration (MIC) less than or equal to the susceptible breakpoint for ZEVTERA against isolates of similar genus or organism group. However, the efficacy of ZEVTERA in treating clinical infections caused by these bacteria has not been established in adequate and well-controlled clinical trials.

Gram-positive bacteria

Staphylococcus epidermidis
Staphylococcus hominis
Staphylococcus lugdunensis
Streptococcus agalactiae
Streptococcus mitis group
Streptococcus dysgalactiae
Streptococcus anginosus group

Gram-negative bacteria

Citrobacter koseri
Enterobacter cloacae
Klebsiella aerogenes
Moraxella catarrhalis
Morganella morganii
Proteus mirabilis

Susceptibility Test Methods

For specific information regarding susceptibility testing methods, interpretive criteria, and associated test methods and quality control standards recognized by FDA for ZEVTERA, see: https://www.fda.gov/STIC.

13 NONCLINICAL TOXICOLOGY

13.1 Carcinogenesis, Mutagenesis, Impairment of Fertility

Carcinogenesis

No animal studies have been performed to evaluate the carcinogenic potential of ZEVTERA as none were warranted.

Mutagenesis

Ceftobiprole medocaril was negative in a standard bacterial reverse mutation test, however, the test was limited by bactericidal activity. Further genetic toxicology studies performed in vitro in mammalian cells showed that both ceftobiprole medocaril (pro-drug) and ceftobiprole (active metabolite) induced mutations at the TK locus in mouse lymphoma L5178Y TK+/- cells, however the pro-drug did not induce mutations in an in vitro HPRT forward mutation assay in CHO cells.

Ceftobiprole medocaril was positive for structural chromosome aberrations in human peripheral blood lymphocytes. When administered intravenously, ceftobiprole medocaril was negative for clastogenic effects in the in vivo mouse bone marrow micronucleus assay.

Impairment of Fertility

Administration of repeated doses of intravenous ceftobiprole medocaril at doses up to 360 mg/kg (approximately 1.4 times the MRHD based on BSA comparisons) to male and female rats starting approximately 2 weeks prior to mating, during mating and continuing through implantation (up to GD 7) were without effect on fertility or early fetal development.

13.2 Animal Toxicology and/or Pharmacology

Both rats and marmosets showed convulsions and thrombi and/or emboli with dosing durations greater than one month. In the 13-week intravenous rat study, clonic convulsions were noted at 500 mg/kg/day (2 times the MRHD based on BSA comparisons) with early deaths seen at 250 mg/kg in the males (1 time the MRHD based on BSA comparison). In the 13-week intravenous marmoset study, convulsions and thrombi were noted at multiple sites distal to the injection site (i.e., lung, and heart) at doses ≥ 50 mg/kg/day (0.1 times the MRHD, based on BSA comparisons). While dogs did not show convulsions in a 13-week toxicology study, catheter patency could only be maintained between 4 to 11 weeks in most animals at doses up to 32 mg/kg/day (0.4 times the MRHD based on BSA comparisons). Fibrin, erythrocytes and inflammatory cells within the lumens of the catheters were noted in the 13-week dog study, while thrombi were observed at the injection site in all species tested. Kidney findings were also noted in the 13-week studies in rats (tubular/duct eosinophilic bodies and presence of foreign material) at 1 times the MRHD.

14 CLINICAL STUDIES

14.1 Staphylococcus aureus Bloodstream Infection (Bacteremia) in Adults

The efficacy of ZEVTERA in the treatment of adult patients with SAB, including right-sided infective endocarditis, was demonstrated in a randomized, controlled, double-blind, multinational, multicenter trial (Trial 1, NCT03138733). In this trial, adult patients were randomized to either ZEVTERA 667 mg (equivalent to 500 mg of ceftobiprole) IV every 6 hours from study Day 1 to Day 8, and 667 mg IV every 8 hours from study Day 9 onwards) or daptomycin (6 mg/kg up to 10 mg/kg IV every 24 hours) plus optional aztreonam for coverage of gram-negative co-infections (the comparator). Randomization was stratified by study site, dialysis status, and use of prior antibacterial drugs. The study was performed in two cohorts based on findings in animal studies [see Nonclinical Toxicology (13.2)]. The initial cohort was enrolled to receive a maximum treatment duration of 28 days. Based on a safety evaluation of cohort 1, patients could be enrolled in cohort 2 to receive a treatment duration of up to 42 days. The duration of study treatment was based on the investigator's clinical evaluation.

Study patients were required to have at least one positive blood culture for S. aureus obtained within 72 hours prior to randomization, signs and symptoms of bacteremia (fever, elevated white blood cell count or immature neutrophils, tachycardia, or hypotension), and at least one of the following conditions of complicated S. aureus bacteremia: chronic dialysis, persistent SAB, acute bacterial skin and skin structure infection, metastatic infections of native tissue, osteomyelitis, epidural or cerebral abscess, or definite native-valve right-sided infective endocarditis by Modified Duke's Criteria. Patients with uncomplicated S. aureus bacteremia, left-sided infective endocarditis, prosthetic heart valves, foreign body material that could not be removed, severe neutropenia, or pneumonia, were excluded from the study.

Upon entry, patients were classified for likelihood of endocarditis using the modified Duke's criteria (definite, possible, or rejected). Echocardiography, including a transesophageal echocardiogram, was to be performed during screening or within 7 days following study enrollment. Final diagnoses were to be made by the study investigators within 7 days of randomization. The final diagnosis for persistent S. aureus bacteremia was made by an independent treatment-blinded Data Review Committee (DRC).

A total of 390 patients (192 ZEVTERA, 198 daptomycin) with SAB were randomized from 60 centers in the USA, Europe, Latin America, and South Africa. The modified ITT (mITT) population was used for the primary efficacy analysis, comprising 387 patients (189 ZEVTERA, 198 daptomycin ± aztreonam) who received study drugs and had a baseline blood culture positive for S. aureus.

Patient demographic and baseline characteristics were balanced between the treatment groups. The median age among the 387 patients in the mITT population was 58 years, ranging from 19 to 91 years), with 31% aged ≥ 65 years, 69% of patients were male, and 96% were White.

Frequent conditions of complicated SAB included acute bacterial skin and skin structure infections (61%), intra-abdominal abscesses (14%), osteoarticular infections (13%), and patients on chronic dialysis (13%). A total of 6.5% of patients had definite right-sided infective endocarditis. A total of 24% had bacteremia caused by methicillin-resistant S. aureus (MRSA).

The primary efficacy outcome in the study was overall success at the post-treatment evaluation (PTE) visit at 70 days post-randomization in the mITT population, as assessed by the independent DRC.

Overall success required survival, symptom improvement, S. aureus bacteremia bloodstream clearance, no new S. aureus bacteremia complications, and no use of other potentially effective antibacterial drugs.

Overall success rates at the PTE visit in the mITT population were 69.8% (132/189) in patients treated with ZEVTERA and 68.7% (136/198) in patients treated with the comparator. The overall primary study outcome and in pre-defined subgroups in the mITT population is shown in Table 12.

Table 12: Data Review Committee Overall Success Rate at the PTE Visit in the mITT Population from the Adult SAB Patients in Trial 1
Group/Subgroup | ZEVTERA n/N (%) | Daptomycin ± aztreonam n/N (%) | Between-group Difference (%) (2-sided 95% CI) [Between-group difference of ZEVTERA minus daptomycin ± aztreonam using Cochran-Mantel-Haenszel weights method adjusted for actual stratum (dialysis status and prior antibacterial treatment use).]
Overall | 132/189 (69.8) | 136/198 (68.7) | 2.0 (−7.1, 11.1)
MSSA (methicillin-susceptible) | 100/141 (70.9) | 97/146 (66.4) | 4.8 (−5.9, 15.5)
MRSA (methicillin-resistant) | 31/45 (68.9) | 38/49 (77.6) | −8.3 (−25.3, 8.6)
ABSSSI | 81/116 (69.8) | 80/121 (66.1) | 4.5 (−7.3, 16.3)
Definite right-sided infective endocarditis | 10/15 (66.7) | 7/10 (70.0) | −6.6 (−40.1, 27.0)

For patients enrolled in Ukraine, overall success rates at the PTE visit in the mITT population were 77/84 (84.1%) in patients treated with ZEVTERA and 82/92 (89.1%) in patients treated with the comparator. For patients enrolled outside Ukraine, overall success rates at the PTE visit in the mITT population were 58/101 (57.4%) in patients treated with ZEVTERA and 54/106 (50.9%) in patients treated with the comparator.

All-cause mortality between randomization and the PTE visit was observed in 17/189 (9.0%) patients treated with ZEVTERA, and 18/198 (9.1%) patients treated with the comparator. Other key secondary efficacy outcomes included microbiological eradication at the PTE visit in the mITT population, which was achieved in 82% of patients treated with ZEVTERA and 77% of patients treated with the comparator, and the development of new S. aureus bacteremia complications, which occurred in 6% of patients treated with ZEVTERA and 6% of patients treated with the comparator. S. aureus bloodstream clearance, defined as 2 consecutive study days with negative blood cultures for S. aureus with no subsequent S. aureus relapse or reinfection, was achieved after a median of 4 days in each treatment group.

S. aureus bloodstream clearance in patients with MSSA was achieved after a median of 3 days in patients treated with ZEVTERA and after a median of 4 days in patients treated with the comparator.

S. aureus bloodstream clearance in patients with MRSA was achieved after a median of 5 days in each treatment group.

Failure of treatment due to relapse of S. aureus bacteremia was assessed by the DRC in two patients (1%) treated with ZEVTERA, and in four patients (2%) treated in the comparator arm. No increase in ceftobiprole MIC was observed for the two isolates from the ZEVTERA-treated patients.

14.2 Acute Bacterial Skin and Skin Structure Infections (ABSSSI) in Adults

The efficacy of ZEVTERA in the treatment of adult patients with ABSSSI was demonstrated in a randomized, controlled, double-blind, multinational, multicenter trial (Trial 2, NCT03137173). Patients were randomized to either ZEVTERA 667 mg (equivalent to 500 mg of ceftobiprole) IV every 8 hours or vancomycin plus aztreonam (vancomycin 1 gram or 15 mg/kg IV every 12 hours, aztreonam 1 gram IV every 12 hours). Randomization was stratified by study site and type of ABSSSI. Treatment duration was 5 to 14 days. Patients could receive concomitant metronidazole for suspected anaerobic infection. A switch to oral therapy was not allowed.

The study enrolled adult patients with ABSSSI (cellulitis/erysipelas, major cutaneous abscess, wound infection) with a lesion area of at least 75 cm^2, systemic or regional signs of infection, and a requirement for IV antibiotic treatment. Patients with other forms of ABSSSI, uncomplicated skin and skin structure infections, or infections related to prosthetic devices, were excluded.

The primary endpoint, assessed in the ITT population, was early clinical response 48–72 hours after start of treatment. The ITT primary analysis population comprised all patients randomized. Early clinical response required a reduction of the primary skin lesion by at least 20%, survival for at least 72 hours, and the absence of concomitant antibacterial treatment or additional unplanned surgery.

The main secondary endpoint was investigator-assessed clinical success at the test-of-cure (TOC) visit 15 to 22 days after randomization and at least 5 days after the end-of-treatment.

A total of 679 patients (335 ZEVTERA, 344 vancomycin plus aztreonam) were randomized from 32 centers in the USA and Europe. The microbiological ITT (mITT) population included 506 patients with at least one valid baseline pathogen.

Patient demographic and baseline characteristics in the ITT population were balanced between the treatment groups. Approximately 95% of patients were classified as White, 59% were male, the median age was 50 years (range: 18 to 89), and the mean body mass index was 28 kg/m^2, 62% of patients were enrolled in the USA, and 38% in Europe. A history of diabetes was present in 11% of patients and current injection drug use was reported in 33% of patients. The types of ABSSSI included cellulitis/erysipelas (33%), wound infection (39%), and major cutaneous abscesses (28%). The median area of the primary skin infection was 259 cm^2.

The primary and main secondary outcomes are shown in Table 13.

Table 13: Primary and Main Secondary Efficacy Outcomes from the Adult Patients with ABSSSI in Trial 2
 | ZEVTERA n/N (%) | Vancomycin plus aztreonam n/N (%) | Between-group Difference (%) (2-sided 95% CI) [Between-group difference of ZEVTERA minus vancomycin plus aztreonam, using Cochran-Mantel-Haenszel weights method adjusted for geographical region and actual type of ABSSSI.]
Primary endpoint analyses [Early clinical response based on at least 20% reduction from baseline in the area of the primary lesion, survival for ≥ 72 hours from the time of administration of the first dose of study drug, no use of concomitant systemic antibacterial treatments or topical antibacterial administration on the primary lesion, and no additional unplanned surgical procedure for the ABSSSI after the start of study treatment.]
Early clinical response at 48–72 hours after start of treatment (ITT) | 306/335 (91.3) | 303/344 (88.1) | 3.3 (−1.2, 7.8)
Main secondary endpoint analysis [Clinical success was defined as complete (cured) or nearly complete (improved) resolution of baseline signs and symptoms of the primary infection, such that no further antibacterial treatment was needed.]
Investigator-assessed clinical success at the TOC visit (ITT) | 302/335 (90.1) | 306/344 (89.0) | 1.0 (−3.5, 5.6)

Clinical response rates at TOC by the most common baseline pathogens in the microbiological ITT (mITT) population, defined as all randomized patients with a baseline pathogen, are presented in Table 14.

Table 14: Primary Efficacy Outcome by Pathogen from the Adult Patients with ABSSSI in Trial 2
 | Early clinical response at 48–72 hours after start of treatment [Early clinical response based on at least a 20% reduction from baseline in the area of the primary lesion, survival for ≥ 72 hours from the time of administration of the first dose of study drug, no use of concomitant systemic antibacterial treatments, or topical antibacterial administration on the primary lesion and no additional unplanned surgical procedure for the ABSSSI after the start of study treatment.] (mITT) |  | Investigator-assessed clinical success at the TOC visit [Clinical success was defined as complete (cured) or nearly complete (improved) resolution of baseline signs and symptoms of the primary infection such that no further antibacterial treatment was needed.] (mITT)
Pathogen | ZEVTERA n/N (%) | Vancomycin plus aztreonam n/N (%) | ZEVTERA n/N (%) | Vancomycin plus aztreonam n/N (%)
Any Gram-positive pathogen | 213/228 (93.4) | 220/244 (90.2) | 203/228 (89.0) | 217/244 (88.9)
Staphylococcus aureus | 186/197 (94.4) | 185/205 (90.2) | 174/197 (88.3) | 180/205 (87.8)
Methicillin-susceptible | 102/108 (94.4) | 112/124 (90.3) | 95/108 (88.0) | 107/124 (86.3)
Methicillin-resistant | 81/86 (94.2) | 67/73 (91.8) | 76/86 (88.4) | 66/73 (90.4)
Streptococcus pyogenes | 17/20 (85.0) | 23/24 (95.8) | 17/20 (85.0) | 22/24 (91.7)
Any Gram-negative pathogen | 26/27 (96.3) | 33/37 (89.2) | 24/27 (88.9) | 34/37 (91.9)
Enterobacterales | 16/16 (100.0) | 24/27 (88.9) | 15/16 (93.8) | 25/27 (92.6)
Klebsiella pneumoniae | 8/8 (100.0) | 5/5 (100.0) | 7/8 (87.5) | 5/5 (100.0)

14.3 Community-Acquired Bacterial Pneumonia

Adult Patients

The efficacy of ZEVTERA in the treatment of adult patients with community-acquired bacterial pneumonia (CABP) was demonstrated in a randomized, controlled, double-blind, multinational, multicenter study (Trial 3, NCT00326287). 638 adults hospitalized with CABP and requiring IV antibacterial treatment for at least 3 days were included in the intent-to-treat (ITT) population, comparing ZEVTERA 667 mg (equivalent to 500 mg of ceftobiprole) IV every 8 hours to ceftriaxone (2 grams IV every 24 hours) with optional linezolid (600 mg IV every 12 hours) for the coverage of resistant gram-positive pathogens, including methicillin-resistant S. aureus (MRSA). Randomization was stratified by Pneumonia Outcomes Research Team (PORT) classification I to III versus IV to V, and by the need for adjunctive treatment with linezolid or matching placebo. The treatment duration was 5–14 days. No adjunctive macrolide therapy was allowed. A switch to oral cefuroxime (500 mg every 12 hours) was allowed after at least 72 hours of IV study treatment for patients who met stringent protocol-specified criteria for improvement and were candidates for hospital discharge.

The study enrolled adult patients hospitalized with CABP based on clinical signs and symptoms, fever and/or leukocytosis/leukopenia, and new radiographic evidence of pulmonary infiltrates. Patients with known bronchial obstruction, pulmonary malignancies, cystic fibrosis, lung abscess, pleural effusion as the primary source of infection, active tuberculosis, or pneumonia known or suspected to be caused by atypical bacteria, were excluded from study participation, as were patients with known or suspected extrapulmonary complications such as concomitant meningitis, endocarditis, septic arthritis, or osteomyelitis.

The ITT primary analysis population comprised all patients randomized. The clinically evaluable (CE) population comprised patients in the ITT population who received at least 48 hours of study medication and met protocol-defined criteria regarding clinical evaluability.

The protocol-specified primary efficacy analyses included clinical cure rates at TOC visit, 7 to 14 days after the end-of-treatment (EOT) in the co-primary ITT and CE populations. The ITT population comprised 638 patients (314 ZEVTERA, 324 ceftriaxone ± linezolid), in 103 centers in the USA, Asia, Europe, and Latin America. The CE population comprised 469 patients, and the microbiological ITT (mITT) population comprised 184 patients with at least one valid baseline pathogen.

Patient demographic and baseline characteristics in the ITT population were balanced between the treatment groups. Approximately 62% of patients were classified as White, and 57% were male. The median age was 56 years (range 18–94). 48% of patients were categorized at baseline as PORT classification III to V, and 22% of patients as PORT classification IV or V. 40% of patients did not receive any prior antibacterial drugs within 30 days of randomization. 12% of patients in the ceftriaxone arm received adjunctive linezolid, and 52% of patients in the ITT population switched to oral antibacterial therapy after at least 72 hours of IV study treatment.

The results for clinical cure at the test-of-cure visit at Day 7 to 14 after end of treatment are shown in Table 15.

Table 15: Clinical Cure at Test of Cure visit, 7 to 14 days After End-of-Treatment, in Adult Patients with CABP in Trial 3
 | ZEVTERA n/N (%) | Ceftriaxone ± Linezolid n/N (%) | Between-group Difference (%) (two-sided 95% CI) [Between-group difference of ZEVTERA minus ceftriaxone ± linezolid. Two-sided 95% CI is based on the Normal approximation to the difference of the two proportions.]
Clinical cure [Clinical cure was defined as survival with resolution of signs and symptoms of the infection or improvement to such an extent that no further antimicrobial therapy was necessary; improvement or stabilization of chest X-ray findings and no receipt of non-study antibacterial treatment for CABP.] at TOC visit (ITT) | 240/314 (76.4) | 257/324 (79.3) | −2.9 (−9.3, 3.6)
Clinical cure at TOC visit (CE) | 200/231 (86.6) | 208/238 (87.4) | −0.8 (−6.9, 5.3)

The 30-day all-cause mortality rates in the ITT population were 5/314 (1.6%) for patients treated with ZEVTERA and 8/324 (2.5%) for patients treated with ceftriaxone ± linezolid.

As this study was designed prior to the current regulatory guidelines, post-hoc re-analyses were conducted to determine the consistency of study results with these guidelines. These post-hoc analyses evaluated an earlier timepoint—clinical success at Day 3—in the ITT population, based on survival and improvement in at least two (with no worsening in any) of the following symptoms: pleuritic chest pain, cough, purulent sputum production or respiratory secretion, and tachypnea.

Clinical success at Day 3 was also evaluated in the following post-hoc-defined analysis populations: 1) Day 3-ITT population, which included 97% (618 of 638) of ITT patients who presented with at least two of the following symptoms at baseline: difficulty breathing, cough, production of purulent sputum, or chest pain; 2) Day 3-modified ITT population, which included patients from the Day 3-ITT population who also met the following criteria at baseline: PORT Risk Class ≥ III, at least two of the following clinical signs—fever, hypothermia, hypotension, tachycardia, and tachypnea, plus at least one of the following: new-onset hypoxemia, rales or pulmonary consolidation, leukocytosis or leukopenia, and new radiographic infiltrates (not related to another disease process) consistent with the diagnosis of bacterial pneumonia; and 3) Day 3-micro ITT population, which was a subset of the Day 3-ITT population who had a valid pathogen at baseline. Results for early clinical success at Day 3 in the Day 3-ITT and Day 3- modified ITT populations are shown in Table 16.

Table 16: Early Clinical Success at Day 3 in Adult Patients with CABP Based on a Post-hoc Analysis of Trial 3
 | ZEVTERA n/N (%) | Ceftriaxone ± linezolid n/N (%) | Between-group Difference (%) (two-sided 95% CI) [Between-group difference of ZEVTERA minus ceftriaxone ± linezolid. Two-sided 95% CI is based on the Normal approximation to the difference of the two proportions.]
Day-3 ITT Population
Clinical Success at Day 3 [Clinical success based on improvement in at least two, with no worsening in any, of the following symptoms: pleuritic chest pain, cough, purulent sputum production or respiratory secretion, tachypnea. Seven patients in the ZEVTERA arm and 13 patients in the comparator arm did not report any of these symptoms and were therefore not included in the ITT population for the analysis evaluating early clinical success at Day 3.] | 218/307 (71.0) | 221/311 (71.1) | -0.1% (-7.2, 7.1)
Day-3 modified ITT Population
Clinical Success at Day 3 | 69/97 (71.1) | 60/90 (66.7)) | 4.5% (−8.8, 17.7)

Clinical response rates at TOC by most common baseline pathogen in the mITT population, defined as all randomized patients with a baseline pathogen, are presented in Table 17.

Table 17: Clinical Cure at Test of Cure Visit and Post-hoc Outcome of Early Clinical Success at Day 3 by Pathogen in Adult CABP Patients in Trial 3
 | Clinical Cure at the TOC visit [Clinical cure was defined as resolution of signs and symptoms of the infection or improvement to such an extent that no further antimicrobial therapy was necessary and improvement or stabilization of chest X-ray findings.] (micro-ITT) |  | Early Clinical Success at Day 3 [Clinical success based on improvement in at least two, with no worsening in any, of the following symptoms: pleuritic chest pain, cough, purulent sputum production or respiratory secretion, tachypnea.] (Day 3 micro-ITT)
Pathogen | ZEVTERA n/N (%) | Ceftriaxone ± linezolid n/N (%) | ZEVTERA n/N (%) | Ceftriaxone ± linezolid n/N (%)
Any Gram-positive pathogen | 37/48 (77.1) | 40/53 (75.5) | 36/46 (78.3) | 35/52 (67.3)
Staphylococcus aureus | 10/14 (71.4) | 6/10 (60.0) | 10/14 (71.4) | 7/10 (70.0)
Methicillin-susceptible | 9/12 (75.0) | 6/10 (60.0) | 8/12 (66.7) | 7/10 (70.0)
Streptococcus pneumoniae | 29/35 (82.9) | 33/41 (80.5) | 27/33 (81.8) | 27/41 (65.9)
Any Gram-negative pathogen | 39/49 (79.6) | 43/51 (84.3) | 35/49 (71.4) | 40/51 (78.4)
Enterobacterales spp. | 14/18 (77.8) | 11/16 (68.8) | 14/18 (77.8) | 13/16 (81.3)
Escherichia coli | 6/6 (100.0) | 1/4 (25.0) | 6/6 (100.0) | 2/4 (50.0)
Klebsiella pneumoniae | 6/8 (75.0) | 7/8 (87.5) | 7/8 (87.5) | 7/8 (87.5)
Haemophilus influenzae | 9/10 (90.0) | 15/16 (93.8) | 4/10 (40.0) | 11/16 (68.8)
Haemophilus parainfluenzae | 6/9 (66.7) | 7/8 (87.5) | 8/9 (88.9) | 8/8 (100.0)

Pediatric Patients (3 months to < 18 Years of Age) with CABP

The efficacy of ZEVTERA in the treatment of pediatric patients 3 months to < 18 years of age with CABP or hospital-acquired bacterial pneumonia (HABP) requiring IV antibacterial drug treatment was demonstrated in a phase 3, randomized, investigator-blinded, active-controlled study (Trial 5, NCT03439124). Although patients with HABP were included in the study, the safety and effectiveness of ZEVTERA for the treatment of HABP have not been established and ZEVTERA is not approved for the treatment of HABP.

138 pediatric patients were randomized in a 2:1 ratio to ZEVTERA 13.3 mg/kg (equivalent to 10 mg/kg of ceftobiprole) to 26.7 mg/kg (equivalent to 20 mg/kg of ceftobiprole - higher than the recommended approved dose) [see Dosage and Administration (2.2, 2.4)]. ZEVTERA was administered by intravenous infusion every 8 hours based on age with a maximum dose of ZEVTERA 667 mg (equivalent to 500 mg of ceftobiprole) (n = 94) or a standard-of-care cephalosporin antibacterial drug (n = 44) for a treatment duration of 7 to 14 days. A switch to an age-appropriate oral antibacterial drug after study Day 3 was allowed.

The primary objective of this study was to evaluate the safety of ZEVTERA. The study was not powered for comparative inferential efficacy analysis, and no efficacy endpoint was identified as primary.

The numbers of patients in the age groups evaluated in the ZEVTERA arm were as follows: 18 pediatric patients aged 12 to < 18 years, 27 pediatric patients aged 6 to < 12 years, 37 pediatric patients aged 2 to < 6 years, and 12 pediatric patients (infants) aged 3 months to < 2 years.

Of the 138 pediatric patients enrolled in the ITT/Safety population, 94% had CABP requiring hospitalization, and 6% had HABP. Patients with ventilator-associated HABP were excluded from the study.

The median treatment duration with ZEVTERA was 6.0 days; 88% of patients treated with ZEVTERA switched to oral antibacterial drugs to complete treatment.

The clinical response was determined at study Day 4, the EOT visit, and at the TOC visit 7 to 14 days after the EOT visit. The ITT population included all patients randomized.

In the ITT population, the clinical response rates for ZEVTERA and the comparator arm were 95.7% and 93.2%, respectively, on Day 4 (between-group difference 2.6% [95% confidence interval (CI): -5.5, 14.7]), 96.8% and 100% at the EOT visit (between-group difference -3.2% [95% CI: -9.1, 5.5]), and 90.4% and 97.7% at the TOC visit (between-group difference -7.3% [95% CI: -15.7, 3.6]).

16 HOW SUPPLIED/STORAGE AND HANDLING

16.1 How Supplied

ZEVTERA (ceftobiprole medocaril sodium for injection), a white, yellowish to slightly brownish sterile powder for reconstitution, is supplied in a single-dose clear glass vial sealed with a rubber stopper (not made with natural rubber latex) and an aluminum seal with a flip-off cap. Each vial contains 667 mg ceftobiprole medocaril sodium (equivalent to 500 mg of ceftobiprole) and is supplied in a carton containing 10 single-dose vials (NDC# 68547-578-10).

16.2 Storage and Handling

Store ZEVTERA vials refrigerated at 2 °C to 8 °C (36 °F to 46 °F) protected from light. Store in carton until time of use.

ZEVTERA must be reconstituted and then further diluted prior to administration by intravenous infusion. Store reconstituted and diluted solution of ZEVTERA as described elsewhere in the labeling [see Dosage and Administration (2.7)].

17 PATIENT COUNSELING INFORMATION

Serious Allergic Reactions

Advise patients (or caregiver) that hypersensitivity reactions were reported with the use of ZEVTERA, and that serious and occasionally fatal serious allergic reactions could occur and require immediate treatment. Advise patients to discontinue ZEVTERA if a hypersensitivity reaction occurs and inform their healthcare provider about any previous hypersensitivity reactions to ZEVTERA, other beta-lactams (including cephalosporins), or other allergens [see Warnings and Precautions (5.2)].

Seizures and Central Nervous System Adverse Reactions

Advise patients (or caregiver) that seizures and other adverse central nervous system (CNS) reactions have been reported during treatment with ZEVTERA. If CNS adverse reactions, including seizures, occur, advise patients to inform their healthcare provider to determine whether ZEVTERA should be discontinued [see Warnings and Precautions (5.3)].

Potentially Serious Diarrhea

Advise patients (or caregiver) that diarrhea is a common problem caused by antibacterial drugs, including ZEVTERA. Sometimes, frequent watery or bloody diarrhea may occur and may be a sign of a more serious intestinal infection. If severe watery or bloody diarrhea develops, instruct patients to contact their healthcare provider [see Warnings and Precautions (5.4)].

Antibacterial Resistance

Patients should be counseled that antibacterial drugs, including ZEVTERA, should be used to treat bacterial infections. They do not treat viral infections (e.g., the common cold). Patients should be told that the medication should be administered exactly as directed [see Warnings and Precautions (5.5)].

Manufactured for:
ISTx, LLC

Distributed by:
La Jolla Pharmaceutical Company, Waltham, MA 02451

Product of Japan.

ZEVTERA is a registered trademark of Basilea Pharmaceutica International Ltd., Allschwil.
Exclusively licensed by Basilea to ISTx, LLC in the USA

PRINCIPAL DISPLAY PANEL - 667 mg Vial Box

NDC# 68547-578-10

Rx Only
10 single-dose vials

ZEVTERA® 667 mg/vial*
(ceftobiprole medocaril sodium for injection)
*equivalent to 500 mg ceftobiprole

For intravenous use only.
Reconstitute and further dilute before use.
Single-dose vial. Discard unused portion.